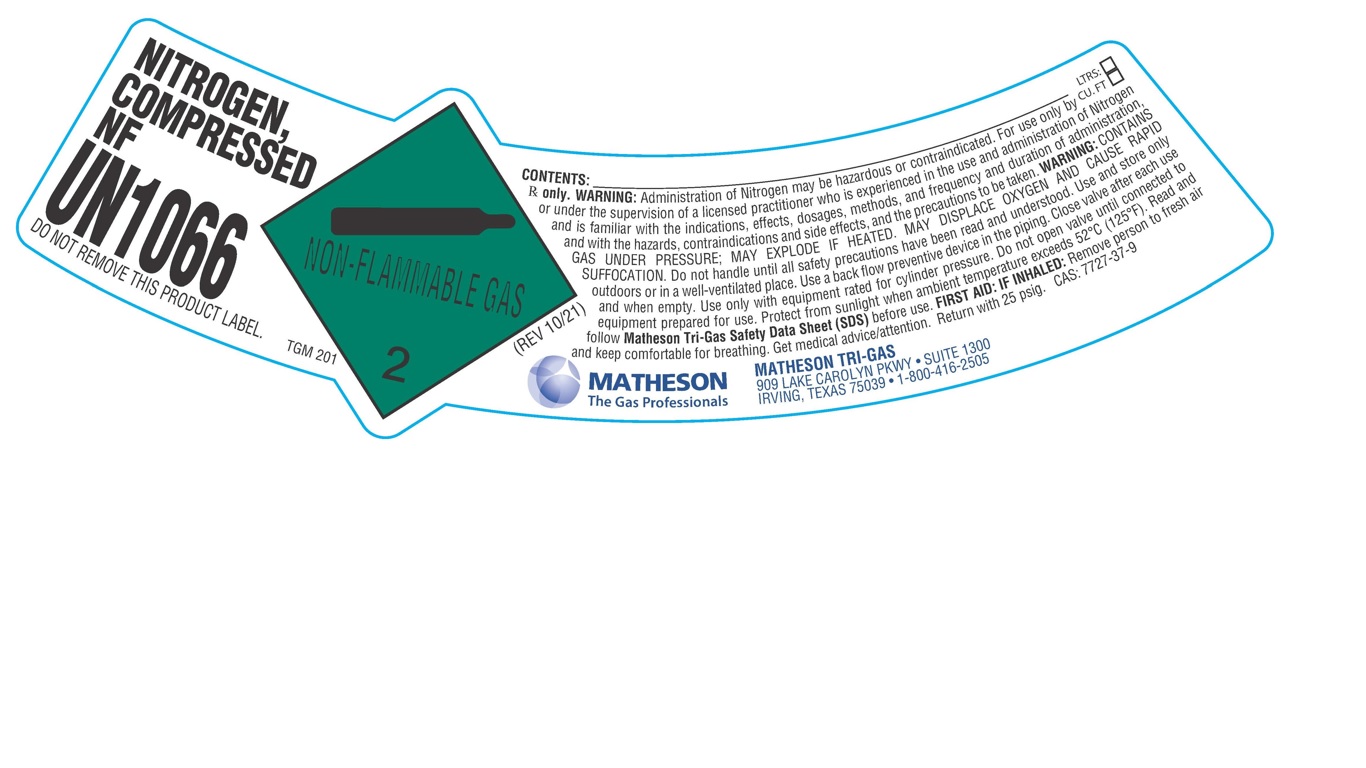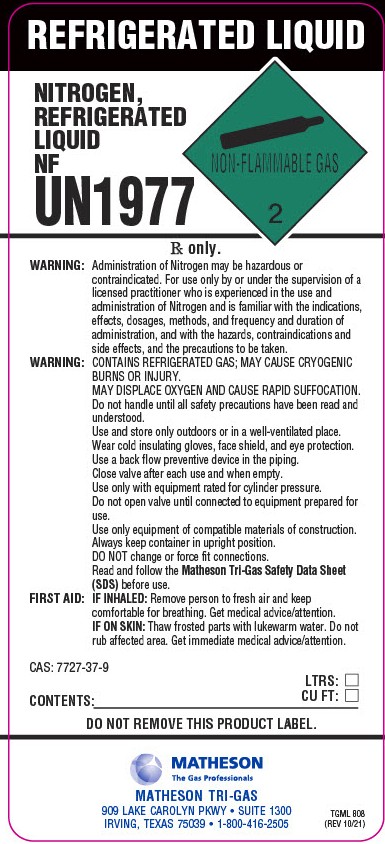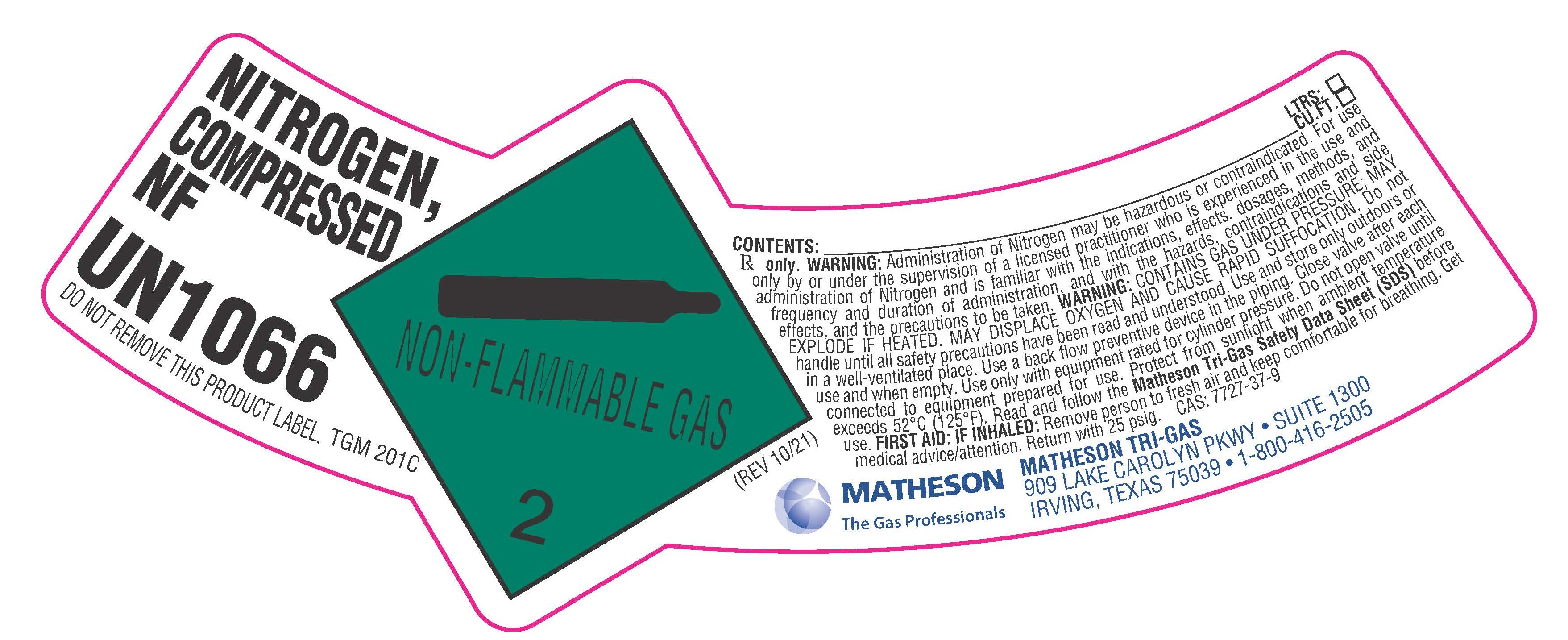 DRUG LABEL: Nitrogen
NDC: 55037-201 | Form: GAS
Manufacturer: Matheson Tri-Gas, Inc.
Category: prescription | Type: HUMAN PRESCRIPTION DRUG LABEL
Date: 20260121

ACTIVE INGREDIENTS: NITROGEN 992 mL/1 L

Nitrogen

PACKAGE LABEL

NITROGEN, COMPRESSED NF

UN1066

DO NOT REMOVE THIS PRODUCT LABEL.

CONTENTS: LTRS: CU.FT.

Rx only. WARNING: Administration of Nitrogen may be hazardous or contraindicated. For use only by or under the supervision of a licensed practitioner who is experienced in the use and administration of Nitrogen and is familiar with the indications, effects, dosages, methods, and frequency and duration of administration, and with the hazards, contraindications and side effects, and the precautions to be taken. WARNING: CONTAINS GAS UNDER PRESSURE; MAY EXPLODE IF HEATED. MAY DISPLACE OXYGEN AND CAUSE RAPID SUFFOCATION. Do not handle until all safety precautions have been read and understood. Use and store only outdoors or in a well-ventilated place. Use a back flow preventive device in the piping. Close valve after each use and when empty. Use only with equipment rated for cylinder pressure. Do not open valve until connected to equipment prepared for use. Protect from sunlight when ambient temperature exceeds 52 C (125 F). Read and follow Matheson Tri-Gas Safety Data Sheet (SDS) before use. FIRST AID: IF INHALED: Remove person to fresh air and keep comfortable for breathing. Get medical advice/attention. Return with 25 psig. CAS: 7727-37-9

MATHESON The Gas Professionals

MATHESON TRI-GAS

909 LAKE CAROLYN PKWY. SUITE 1300

IRVING, TEXAS 75039 . 1-800-416-2505

PACKAGE LABEL

NITROGEN, COMPRESSED NF

UN1066

DO NOT REMOVE THIS PRODUCT LABEL.

CONTENTS: LTRS: CU.FT.

Rx only. WARNING: Administration of Nitrogen may be hazardous or contraindicated. For use only by or under the supervision of a licensed practitioner who is experienced in the use and administration of Nitrogen and is familiar with the indications, effects, dosages, methods, and frequency and duration of administration, and with the hazards, contraindications and side effects, and the precautions to be taken. WARNING: CONTAINS GAS UNDER PRESSURE; MAY EXPLODE IF HEATED. MAY DISPLACE OXYGEN AND CAUSE RAPID SUFFOCATION. Do not handle until all safety precautions have been read and understood. Use and store only outdoors or in a well-ventilated place. Use a back flow preventive device in the piping. Close valve after each use and when empty. Use only with equipment rated for cylinder pressure. Do not open valve until connected to equipment prepared for use. Protect from sunlight when ambient temperature exceeds 52 C (125 F). Read and follow the Matheson Tri-Gas Safety Data Sheet (SDS) before use. FIRST AID: IF INHALED: Remove person to fresh air and keep comfortable for breathing. Get medical advice/attention. Return with 25 psig. CAS: 7727-37-9

MATHESON The Gas Professionals

MATHESON TRI-GAS

909 LAKE CAROLYN PKWY. SUITE 1300

IRVING, TEXAS 75039 . 1-800-416-2505

PACKAGE LABEL

REFRIGERATED LIQUID

NITROGEN, REFRIGERATED LIQUID NF

UN1977

Rx only.

WARNING: Administration of Nitrogen may be hazardous or contraindicated. For use only by or under the supervision of a licensed practitioner who is experienced in the use and administration of Nitrogen and is familiar with the indications, effects, dosages, methods, and frequency and duration of administration, and with the hazards, contraindications and side effects, and the precautions to be taken.

WARNING: CONTAINS REFRIGERATED GAS; MAY CAUSE CRYOGENIC BURNS OR INJURY. MAY DISPLACE OXYGEN AND CAUSE RAPID SUFFOCATION.

Do not handle until all safety precautions have been read and understood. Use and store only outdoors or in a well-ventilated place. Wear cold insulating gloves, face shield, and eye protection. Use a back flow preventive device in the piping. Close valve after each use and when empty. Use only with equipment rated for cylinder pressure. Do not open valve until connected to equipment prepared for use. Use only with equipment of compatible materials of construction. Always keep container in upright position. DO NOT change or force fit connections. Read and follow the Matheson Tri-Gas Safety Data Sheet (SDS) before use.

FIRST AID: IF INHALED: Remove person to fresh air and keep comfortable for breathing. Get medical advice/attention.

IF ON SKIN: Thaw frosted parts with lukewarm water. Do not rub affected area. Get immediate medical advice/attention.

CAS: 7727-37-9

CONTENTS: LTRS: CU FT:

DO NOT REMOVE THIS PRODUCT LABEL.

MATHESON The Gas Professionals

MATHESON TRI-GAS

909 LAKE CAROLYN PKWY. SUITE 1300

IRVING, TEXAS 75039 . 1-800-416-2505